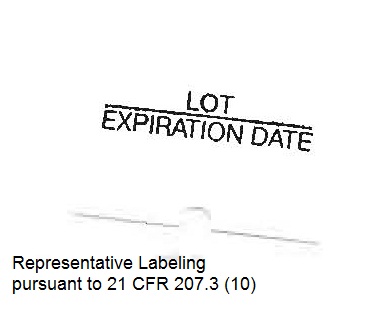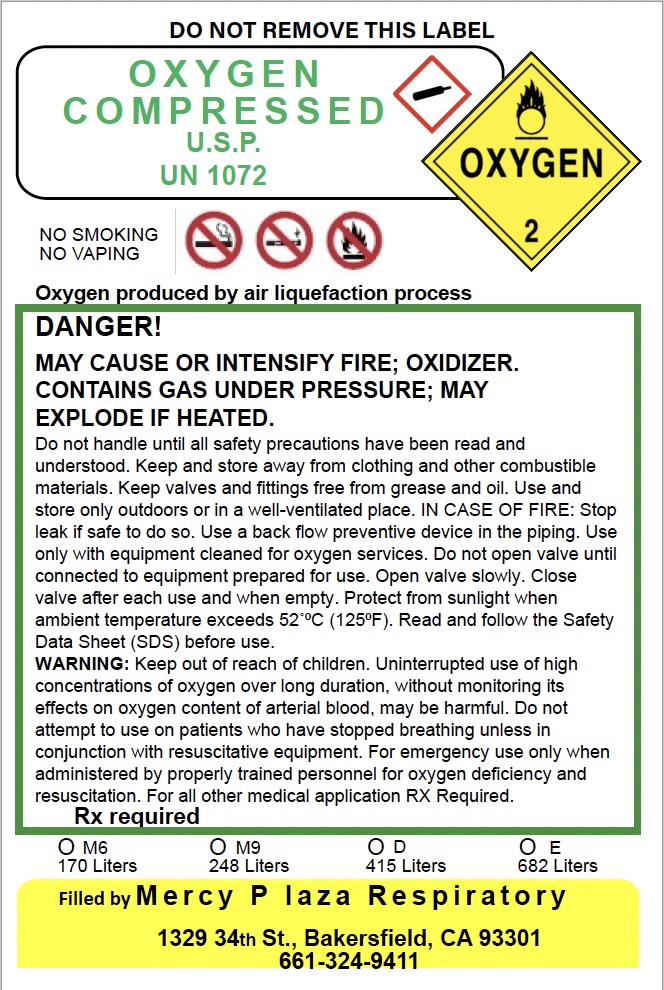 DRUG LABEL: Oxygen
NDC: 73055-001 | Form: GAS
Manufacturer: West Healthcare Solutions, Inc dba Mercy Plaza Respiratory & Medical Supply
Category: prescription | Type: HUMAN PRESCRIPTION DRUG LABEL
Date: 20251120

ACTIVE INGREDIENTS: OXYGEN 99 L/100 L

Oxygen, USP

Principal for Oxygen Product

DO NOT REMOVE THIS LABEL

O X Y G E N
C O M P R E S S E D

U.S.P.
UN 1072

Oxygen produced by air liquefaction process
DANGER!
MAY CAUSE OR INTENSIFY FIRE; OXIDIZER.
CONTAINS GAS UNDER PRESSURE; MAY EXPLODE IF HEATED.

Do not handle until all safety precautions have been read and understood. Keep and store away from clothing and other combustible materials. Keep valves and fittings free from grease and oil. Use and store only outdoors or in a well-ventilated place. IN CASE OF FIRE: Stop leak if safe to do so. Use a back flow preventive device in the piping. Use only with equipment cleaned for oxygen services. Do not open valve until connected to equipment prepared for use. Open valve slowly. Close valve after each use and when empty. Protect from sunlight when ambient temperature exceeds 52°C (125°F). Read and follow the Safety Data Sheet (SDS) before use.

WARNING: Keep out of reach of children. Uninterrupted use of high concentrations of oxygen over long duration, without monitoring its effects on oxygen content of arterial blood, may be harmful. Do not attempt to use on patients who have stopped breathing unless in conjunction with resuscitative equipment. For emergency use only when administered by properly trained personnel for oxygen deficiency and resuscitation. For all other medical application RX Required.

Rx required

Filled by Mercy Plaza Respiratory
1329 34th St., Bakersfield, CA 93301
661-324-9411

NO SMOKING
NO VAPING

M6 M9 D E
170 Liters 248 Liters 415 Liters 682 Liters